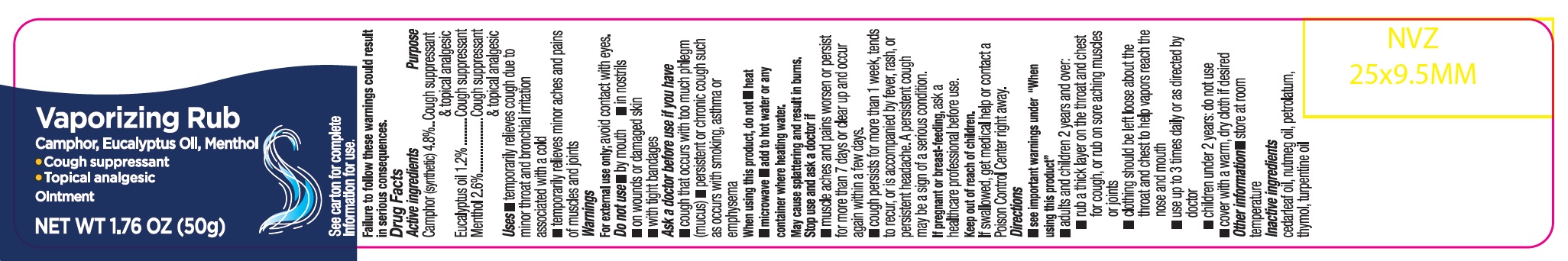 DRUG LABEL: Vaporizing Rub
NDC: 73492-716 | Form: OINTMENT
Manufacturer: ALAINA HEALTHCARE PRIVATE LIMITED
Category: otc | Type: HUMAN OTC DRUG LABEL
Date: 20251209

ACTIVE INGREDIENTS: CAMPHOR (SYNTHETIC) 2.4 g/50 g; MENTHOL 1.3 g/50 g; EUCALYPTUS OIL 0.6 g/50 g
INACTIVE INGREDIENTS: CEDAR LEAF OIL; NUTMEG OIL; PETROLATUM; THYMOL; TURPENTINE OIL

Vaporizing Rub

Drug Facts

Active ingredient Purpose

Camphor (synthetic) 4.8% ....................................................................Cough suppressant & topical analgesic

Eucalyptus Oil 1.2% .............................................................................Cough suppressant

Menthol 2.6% .......................................................................................Cough suppressant & topical analgesic

Uses:

- temporarily relieves cough due to minor throat and bronchial irritation associated with a cold
- temporarily relieves minor aches and pains of muscles and joints

Warnings

For external use only; avoid contact with eyes.

Do not use

- by mouth
- in nostrils
- on wounds or damaged skin
- with tight bandages

Ask a doctor before use if you have

- cough that occurs with too much phlegm (mucus)
- persistent or chronic cough such as occurs with smoking, asthma or emphysema

When using this product, do not

- heat
- microwave
- add to hot water or any container where heating water.

May cause splattering and result in burns. Stop use and ask a doctor if

- muscle aches and pains worsen or persist for more than 7 days or clear up and occur again within a few days.
- cough persists for more than 1 week, tends to recur, or is accompanied by fever, rash, or persistent headache. A persistent cough may be a sign of a serious condition.

If pregnant or breast-feeding,ask a healthcare professional before use.

Keep out of reach of children

If swallowed, get medical help or contact a Poison Control Center right away.

Directions:

- see important warnings under "When using this product"
- adults and children 2 years and over:
- rub a thick layer on the throat and chest for cough, or rub on sore aching muscles or joints
- clothing should be left loose about the throat and chest to help vapors reach the nose and mouth
- use up to 3 times daily or as directed by doctor
- children under 2 years: do not use
- cover with a warm, dry cloth if desired

Other information

- store at room temperature

Inactive Ingredients

cedarleaf oil, nutmeg oil, petrolatum, thymol, turpentine oil

PACKAGE LABEL

PRINCIPAL DISPLAY PANEL

Vaporizing Rub

Camphor, Eucalyptus Oil, Menthol

• Cough Suppressant

• Topical Analgesic

Ointment

NET WT 1.76 OZ (50g)